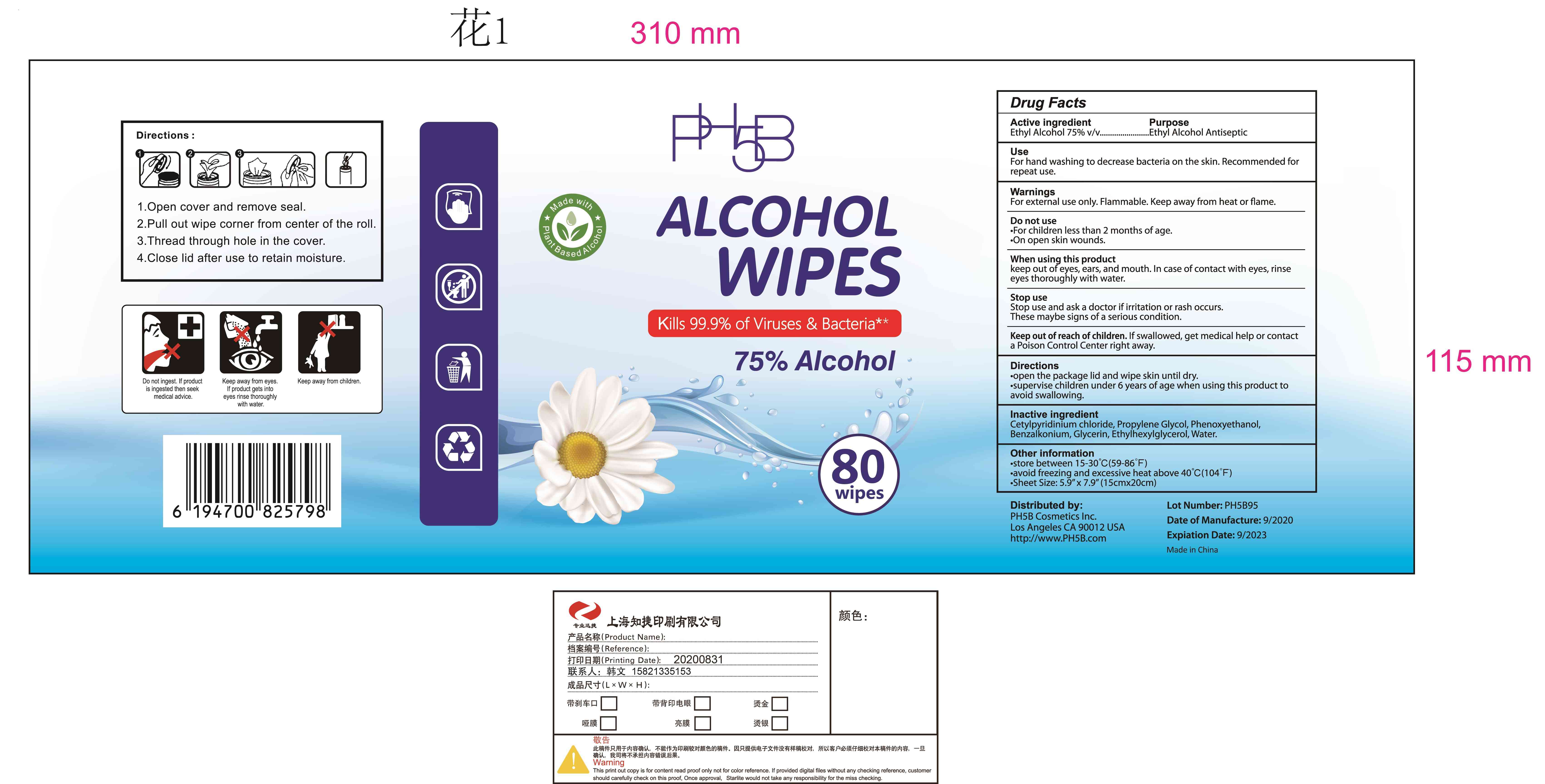 DRUG LABEL: sanitizing wipes
NDC: 42003-203 | Form: CLOTH
Manufacturer: Zhejiang Jiayan Daily Commodity Co., Ltd
Category: otc | Type: HUMAN OTC DRUG LABEL
Date: 20220225

ACTIVE INGREDIENTS: ALCOHOL 75 mL/100 1
INACTIVE INGREDIENTS: WATER; CETYLPYRIDINIUM CHLORIDE; CHAMOMILE; PHENOXYETHANOL; GLYCERIN; ETHYLHEXYLGLYCERIN; BENZALKONIUM CHLORIDE

42003-203
sanitizing wipes

Active Ingredient(s)

Ethyl Alcohol 75% v/v

Purpose

Ethyl Alcohol Antiseptic

Use

For hand washing to decrease bacteria on the skin. Recommended for repeat use.

Warnings

For external use only. Flammable. Keep away from heat or flame.

Do not use
For children less than 2 months of age.
On open skin wounds.

When using this product
keep out of eyes, ears, and mouth. In case of contact with eyes, rinse eyes thoroughly with water.

Stop use
Stop use and ask a doctor if irritation or rash occurs.
These maybe signs of a serious condition.

Keep out of reach of children. If swallowed, get medical help or contact a Poison Control Center rig ht away.

Do not use

For children less than 2 months of age.
On open skin wounds.

When using this product
keep out of eyes, ears, and mouth. In case of contact with eyes, rinse eyes thoroughly with water.

Stop use
Stop use and ask a doctor if irritation or rash occurs.
These maybe signs of a serious condition.

Keep out of reach of children. If swallowed, get medical help or contact a Poison Control Center rig ht away.

Stop use
Stop use and ask a doctor if irritation or rash occurs.
These maybe signs of a serious condition.

Keep out of reach of children. If swallowed, get medical help or contact a Poison Control Center rig ht away.

Directions

open the package lid and wipe skin until dry.
supervise children under 6 years of age when using this product to avoid swallowing.

Other information

store between 15-30°C (59-86°F)
avoid freezing and excessive heat above 40°C (l04°F)
Sheet Size: 5.9" x 7.9" (15cm*20cm)

Inactive ingredients

Cetylpyridinium chloride, Propylene Glycol, Phenoxyethanol, Benzalkonium, Glycerin, Ethylhexylglycerol, Water.